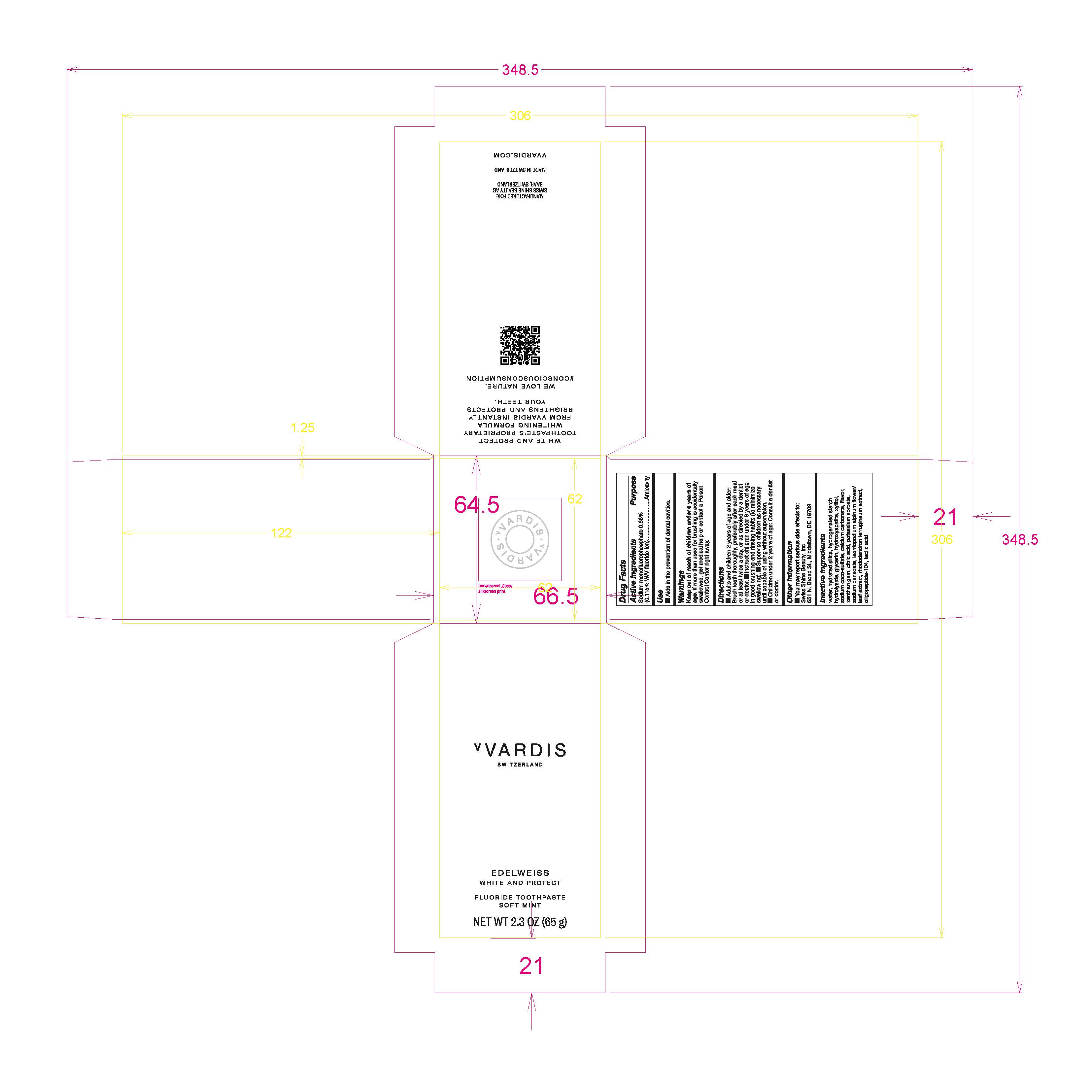 DRUG LABEL: Fluoride Soft Mint
NDC: 79763-003 | Form: PASTE, DENTIFRICE
Manufacturer: Swiss Shine Beauty AG
Category: otc | Type: HUMAN OTC DRUG LABEL
Date: 20210819

ACTIVE INGREDIENTS: SODIUM MONOFLUOROPHOSPHATE 0.88 g/100 g
INACTIVE INGREDIENTS: POTASSIUM SORBATE; TRIBASIC CALCIUM PHOSPHATE; XYLITOL; SODIUM COCO-SULFATE; XANTHAN GUM; CITRIC ACID MONOHYDRATE; LACTIC ACID; CALCIUM CARBONATE; WATER; HYDROGENATED STARCH HYDROLYSATE; GLYCERIN; SODIUM BENZOATE; LEONTOPODIUM ALPINUM FLOWERING TOP; HYDRATED SILICA; RHODODENDRON FERRUGINEUM WHOLE

Fluoride Toothpaste Soft Mint

Active Ingredients

Sodium monofluorophosphate 0.88% (0.115% W/V fluoride Ion)

Purpose Anticavity

Use

- Aids in the prevention of dental cavities.

Keep out of reach of children under 6 years age.

If more than used for brushing is accidently swallowed, get medical help or contact a Poison Control Center right away.

Use
Aids in the prevention of dental cavities.

Warnings

Keep our of reach of children under 6 years of age. If more than used for brushing is accidentally swallowed, get medical help or contact a Poison Control Center right away.

Directions

- Adults and children 2 years of age and older: Brush teeth thoroughly, preferably after each meal or at least twice a day, or as directed by a dentist or doctor.
- Instruct children under 6 years of age in good brushing and rinsing habits (to minimize swallowing).
- Supervise children as necessary until capable of using without supervision.
- Children under 2 years of age: Consult a dentist or doctor.

Inactive Ingredients

water, hydrated silica, hydrogenated strach hydrolysate, glycerin, hydroxyapatite, xylitol, sodium coco-sulfate, calcium carbonate, flavor, xanthan gum, citric acid, potasium sorbate, sodium benzoate, leontopodium alpinum flower/leaf extract, rhododendron ferrugineum extract, oligopeptide-104, lactic acid

Other Information

You may report serious side effects to : Swiss Shine Beauty, Inc.

651 N. Broad St., Middletown, DE 19709

PACKAGE LABEL

vVARDIS

SWITZERLAND

EDELWEISS

WHITE AND PROTECT

FLUORIDE TOOTHPASTE

SOFT MINT

NET WT 2.3OZ (65 g)